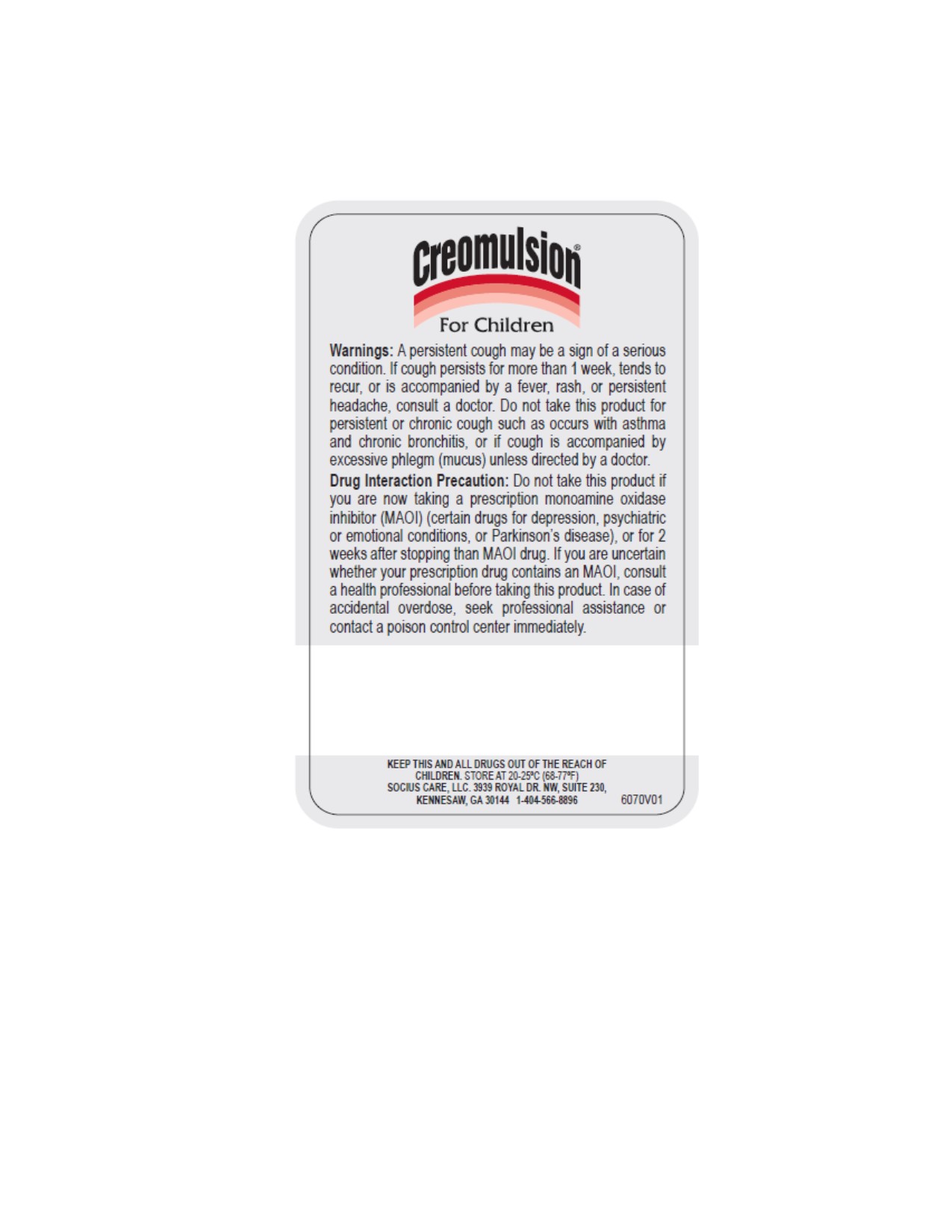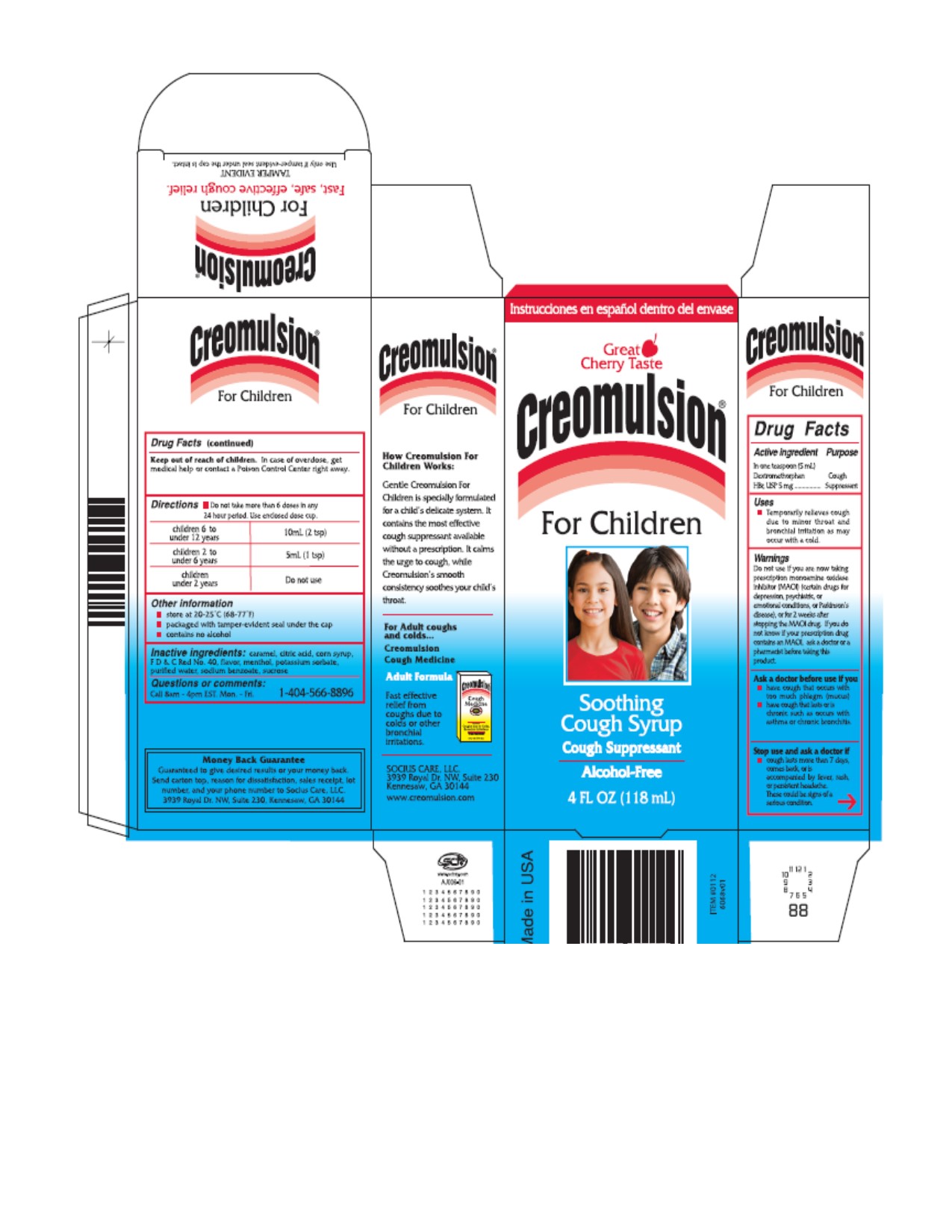 DRUG LABEL: Creomulsion
NDC: 70893-0012 | Form: SYRUP
Manufacturer: Socius Care, LLC
Category: otc | Type: HUMAN OTC DRUG LABEL
Date: 20260217

ACTIVE INGREDIENTS: DEXTROMETHORPHAN HYDROBROMIDE 5 mg/5 mL
INACTIVE INGREDIENTS: CARAMEL; CITRIC ACID MONOHYDRATE; CORN SYRUP; FD&C RED NO. 40; MENTHOL; POTASSIUM SORBATE; WATER; SODIUM BENZOATE; SUCROSE

Creomulsion For Children Soothing Cough Syrup Drug Facts

Active Ingredient

In one teaspoon (5 ml) Dextromethorphan HBr, USP 5 mg

Purpose

Cough Suppressant

Uses

- Temporarily relieves cough due to minor throat and bronchial irritation as may occur with a cold.

Warnings

Do not use if you are now taking prescription monoamine oxidase inhibitor (MAOI)

(certain drugs for depression, psychiatric, or emotional conditions, or Parkinson's disease)

or for 2 weeks after stopping the MAOI drug. If you do not know if your prescription drug contains an MAOI, ask a doctor or a pharmacist before taking the product.

Ask a doctor before use if you

- have cough that occurs with too much phlegm (mucus)

- have cough that lasts or is chronic such as occurs with smoking, asthma, chronic bronchitis, or emphysema.

Stop use and ask a doctor if

- cough lasts more than 7 days comes back, or is accompanied by fever, rash, or persistent headache. These could be signs of a serious condition.

PREGNANCY OR BREAST FEEDING

If pregnant or breast feeding, ask a health professional before use.

Keep out of reach of children. In case of overdose, get medical help or contact a Poison Control Center right away.

Directions

- Do not take more than 6 doses in any 24 period. Use enclosed dose cup.

Children 6 years to under 12 years | 10mL (2tsp) every 4 hours
Children 2 to under 6 years | 5mL (1tsp) every 4 hours
Children under 2 years | Do not use

Other Information

- store at 20-25°C (68-77°F)

- packaged with tamper evident seal around cap

- contains no alcohol

Inactive Ingredients

caramel, citric acid, corn syrup, FD and C Red No. 40, flavor, menthol, potassium sorbate, purified water, sodium benzoate, sucrose

Questions or Comments

Call 8am - 4pm Est. Mon - Fri. 1-404-566-8896

Money Back Guarantee

Guaranteed to give desired results or your money back.

Send carton top, reason for dissatisfaction, sales receipt, lot number, and your phone number to Socius Care, LLC

3939 Royal Dr. NW, Suite 230, Kennesaw, GA 30144

DESCRIPTION

How Creomulsion For Children Works?

Gentle Creomulsion For Children is specially formulated for a child's delicate system. It contains the most effective cough suppressant available without a prescription. It calms the urge to cough, while Creomulsion's smooth consistency soothes your child's throat.